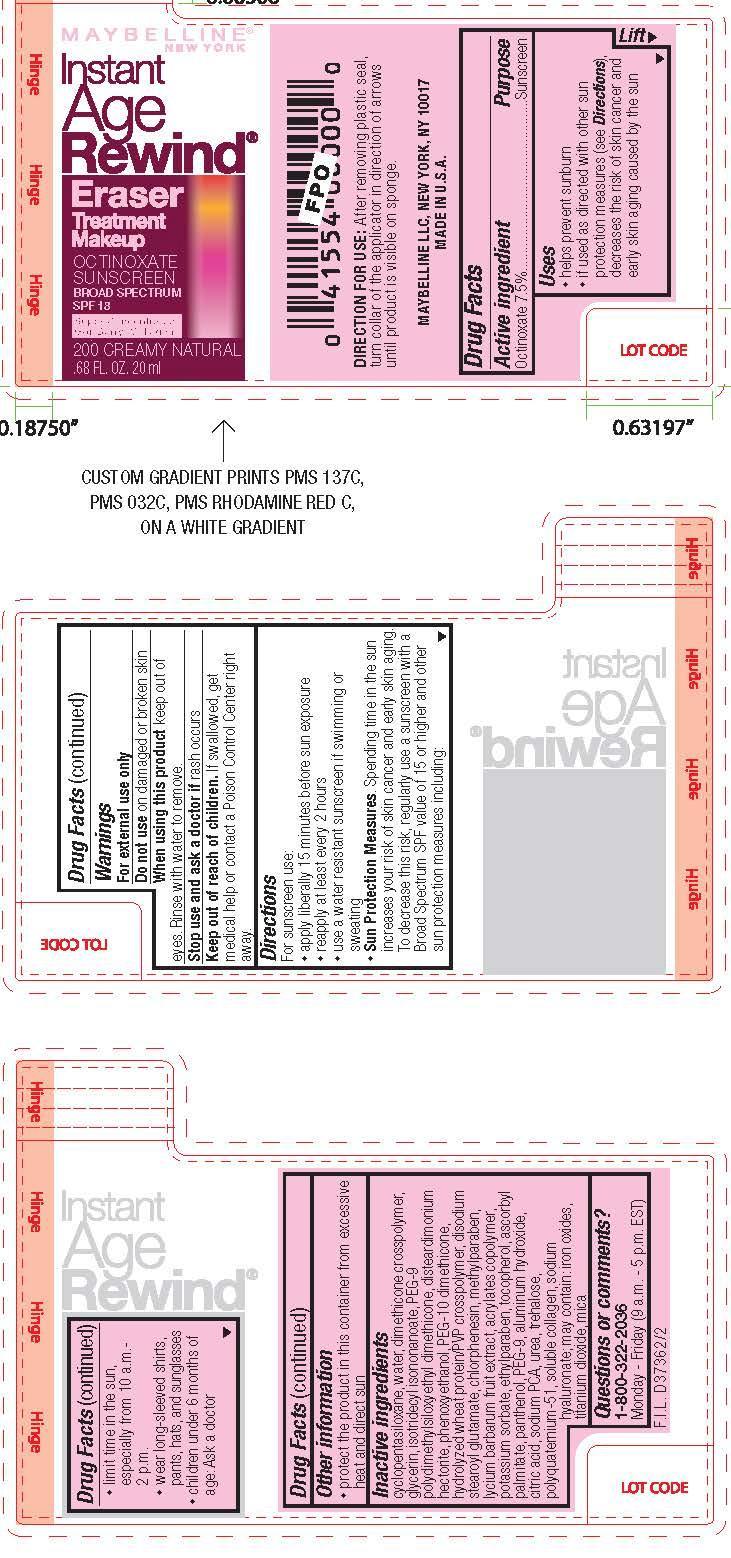 DRUG LABEL: Maybelline New York Instant Age Rewind Eraser Treatment Makeup Broad Spectrum SPF 18 Sunscreen
NDC: 49967-007 | Form: LOTION
Manufacturer: L'Oreal USA Products Inc
Category: otc | Type: HUMAN OTC DRUG LABEL
Date: 20231228

ACTIVE INGREDIENTS: OCTINOXATE 75 mg/1 mL
INACTIVE INGREDIENTS: WATER; GLYCERIN; PHENOXYETHANOL

Drug Facts

Active ingredient

Octinoxate 7.5%

Purpose

Sunscreen

Uses

- helps prevent sunburn
- if used as directed with other sun protection measures (see Directions), decreases the risk of skin cancer and early skin aging caused by the sun

Warnings

For external use only

Do not use

on damaged or broken skin

When using this product

keep out of eyes. Rinse with water to remove.

Stop use and ask a doctor if

rash occurs

Keep out of reach of children.

If swallowed, get medical help or contact a Poison Control Center right away.

Directions

For sunscreen use:

● apply liberally 15 minutes before sun exposure

● reapply at least every 2 hours

● use a water resistant sunscreen if swimming or sweating

● Sun Protection Measures. Spending time in the sun increases your risk of skin cancer and early skin aging. To decrease this risk, regularly use a sunscreen with a Broad Spectrum SPF value of 15 or higher and other sun protection measures including:

● limit time in the sun, especially from 10 a.m. – 2 p.m.

● wear long-sleeved shirts, pants, hats, and sunglasses

● children under 6 months of age: Ask a doctor

Other information

- protect the product in this container from excessive heat and direct sun

Questions or comments?

1-800-322-2036

Monday - Friday (9 a.m. - 5 p.m. EST)

Inactive ingredients

cyclopentasiloxane, water, dimethicone crosspolymer, glycerin, isotridecyl isononanoate, PEG-9 polydimethylsiloxyethyl dimethicone, disteardimonium hectorite, phenoxyethanol, PEG-10 dimethicone, hydrolyzed wheat protein/PVP crosspolymer, disodium stearoyl glutamate, chlorphenesin, methylparaben, lycium barbarum fruit extract, acrylates copolymer, potassium sorbate, ethylparaben, tocopherol, ascorbyl palmitate, panthenol, PEG-9, aluminum hydroxide, citric acid, sodium PCA, urea, trehalose, polyquaternium-51, soluble collagen, sodium hyaluronate; may contain: iron oxides, titanium dioxide, mica